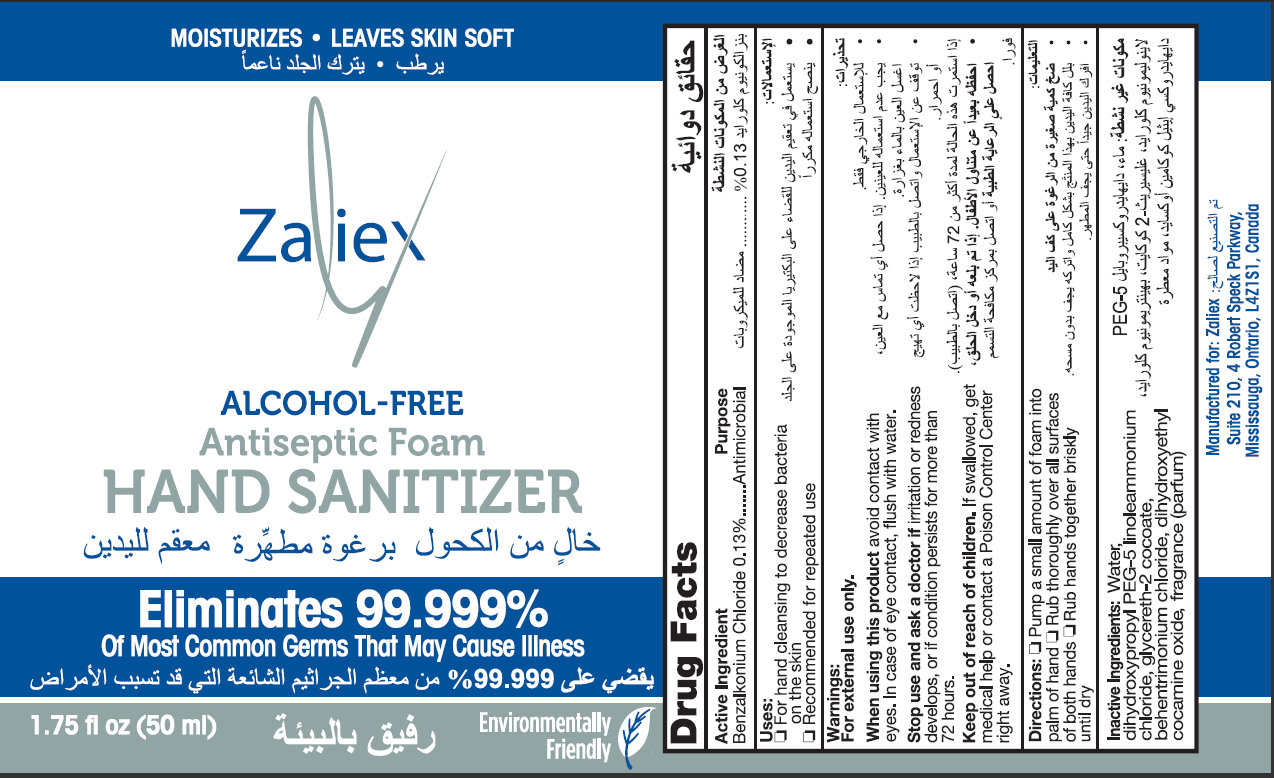 DRUG LABEL: Zaliex ALCOHOL-FREE Antiseptic Hand Sanitizer
NDC: 76452-001 | Form: LIQUID
Manufacturer: SAS Healthcare Inc
Category: otc | Type: HUMAN OTC DRUG LABEL
Date: 20111026

ACTIVE INGREDIENTS: BENZALKONIUM CHLORIDE 0.13 mL/100 mL
INACTIVE INGREDIENTS: WATER; DIHYDROXYPROPYL PEG-5 LINOLEAMMONIUM CHLORIDE; GLYCERETH-2 COCOATE; BEHENTRIMONIUM CHLORIDE; DIHYDROXYETHYL COCAMINE OXIDE

Zaliex ALCOHOL-FREE Antiseptic Foam Hand Sanitizer

Active Ingredient

Benzalkonium Chloride 0.13%

Purpose

Antimicrobial

Uses:

- For hand cleansing to decrease bacteria on the skin
- Recommended for repeated use

Warnings:

For external use only.

When using this product avoid contact with eyes. In case of eye contact, flush with water.

Stop use and ask a doctor if irritation or redness develops, or if condition persists for more than 72 hours.

Keep out of reach of children. If swallowed, get medical help or contact a Poison Control Center right away.

Directions:

- Pump a small amount of foam into palm of hand
- Run thoroughly over all surfaces of both hands
- Rub hands together briskly until dry

Inactive Ingredients:

Water, dihydroxypropyl PEG-5 linoleammonium chloride, glycereth-2 cocoate, behentrimonium chloride, dihydroxyethyl cocamine oxide, fragrance (parfum)

Manufactured for:

Zaliex

Suite 210, 4 Robert Speck Parkway,

Mississauga, Ontario, L4Z1S1, Canada

Zaliex ALCOHOL-FREE Antiseptic Foam Hand Sanitizer 50ml

MOISTURIZES * LEAVES SKIN SOFT
Zaliex
ALCOHOL-FREE
Antiseptic Foam
HAND SANITIZER
Eliminates 99.999%
Of Most Common Germs That May Cause Illness
1.75 fl oz (50 ml)
Environmentally Friendly